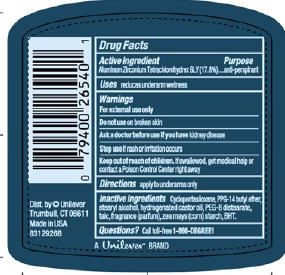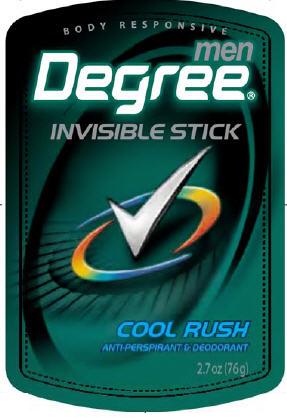 DRUG LABEL: Degree for Men Cool Rush
NDC: 64942-1096 | Form: STICK
Manufacturer: Conopco Inc. d/b/a Unilever
Category: otc | Type: HUMAN OTC DRUG LABEL
Date: 20100323

ACTIVE INGREDIENTS: Aluminum Zirconium Tetrachlorohydrex GLY 17.8 g/100 g

Degree for Men Cool Rush Antiperspirant and Deodorant PDP and drug facts

Active ingredient Purpose

Aluminum Zirconium Tetrachlorohydrex GLY(17.8%)............anti-perspirant

Warning
For external use only

Do not use on broken skin

Ask a doctor before use if you have kidney disease

Stop use if rash or irritation occurs

Keep out of reach of children. If swallowed, get medical help or contact a Poison Control Center right away.

Inactive ingredients

Cyclopentasiloxane, PPG-14 Butyl Ether, Stearyl Alcohol, Hydrogenated Castor Oil, PEG-8 Distearate, Talc, Fragrance (Parfum), BHT, Zea Mays (Corn) Starch.

Questions? Call toll-free 1-866-DEGREE1

PACKAGE LABEL

PDP 2.7 oz front

PACKAGE LABEL

PDP 2.7 oz back